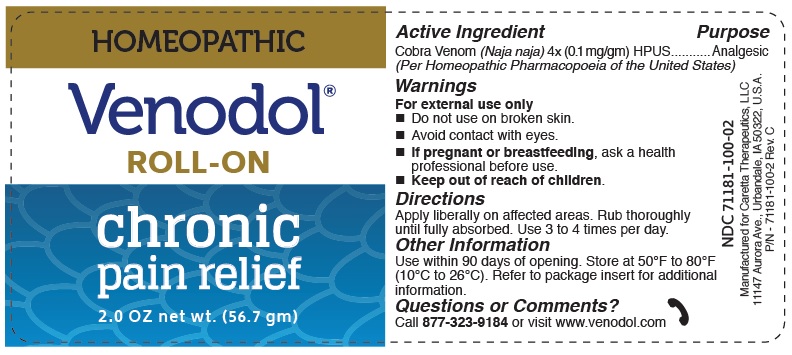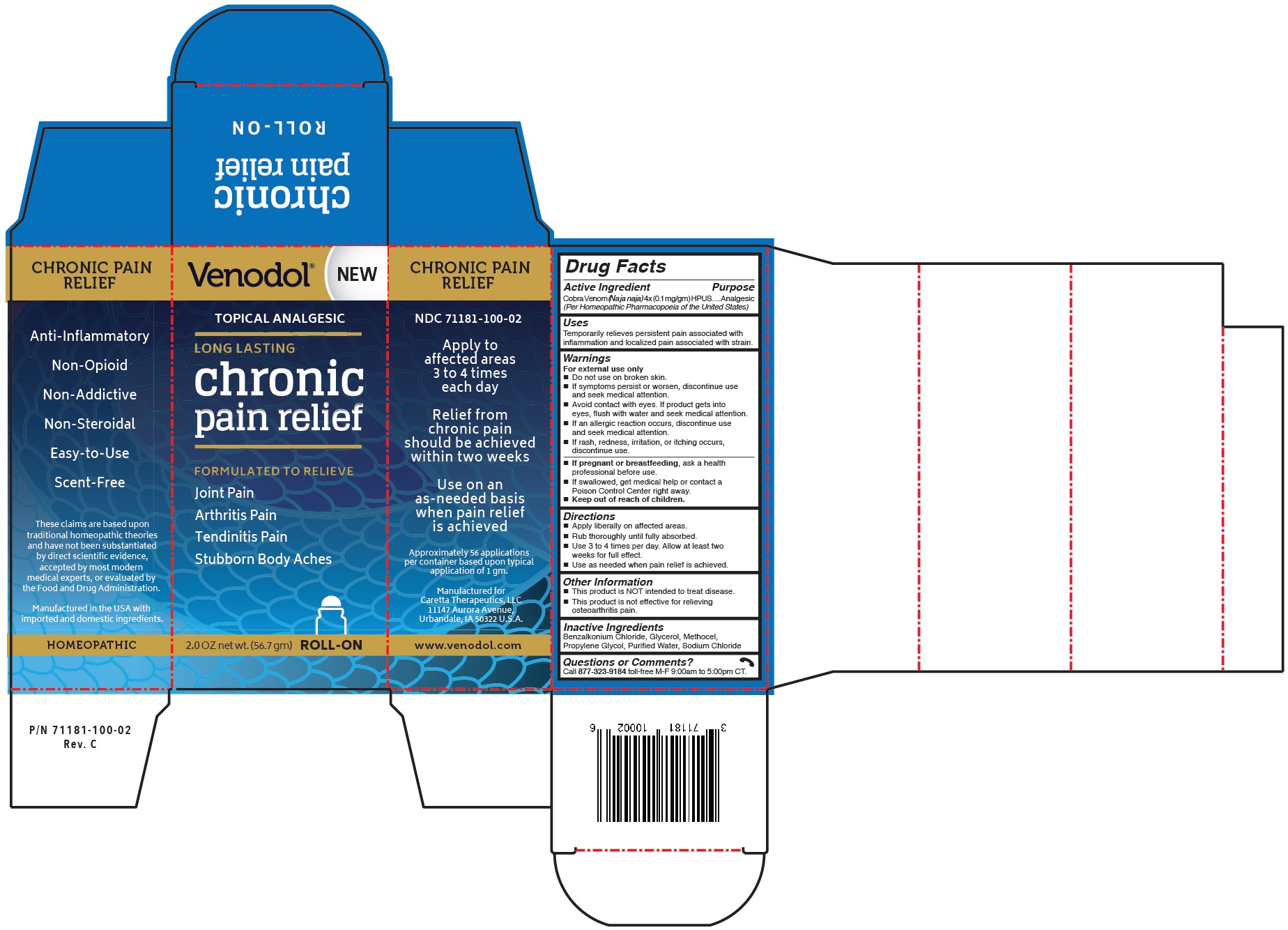 DRUG LABEL: Venodol
NDC: 71181-100 | Form: LOTION
Manufacturer: Caretta Therapeutics
Category: homeopathic | Type: HUMAN OTC DRUG LABEL
Date: 20180323

ACTIVE INGREDIENTS: NAJA NAJA VENOM 4 [hp_X]/1 mL
INACTIVE INGREDIENTS: BENZALKONIUM CHLORIDE 0.0001 g/1 mL; GLYCERIN 0.2 mL/1 mL; HYPROMELLOSES 0.01 g/1 mL; PROPYLENE GLYCOL 0.2 mL/1 mL; SODIUM CHLORIDE 0.001 g/1 mL

Venodol™ Homeopathic Chronic Pain Relief

Drug Facts

ACTIVE INGREDIENT

Active Ingredient | Purpose
Cobra Venom (Naja naja) 4x (0.1 mg/gm) HPUS.... | Analgesic
(Per Homeopathic Pharmacopoeia of the United States)

Uses

Temporarily relieves persistent pain associated with inflammation and localized pain associated with strain.

Warnings

For external use only

- Do not use on broken skin.
- If symptoms persist or worsen, discontinue use and seek medical attention.
- Avoid contact with eyes. If product gets into eyes, flush with water and seek medical attention.
- If an allergic reaction occurs, discontinue use and seek medical attention.
- If rash, redness, irritation, or itching occurs, discontinue use.
- If pregnant or breastfeeding, ask a health professional before use.
- If swallowed, get medical help or contact a Poison Control Center right away.

- Keep out of reach of children.

Directions

- Apply liberally on affected areas.
- Rub thoroughly until fully absorbed.
- Use 3 to 4 times per day. Allow at least two weeks for full effect.
- Use as needed when pain relief is achieved.

Other Information

- This product is NOT intended to treat disease.
- This product is not effective for relieving osteoarthritis pain.

Inactive Ingredients

Benzalkonium Chloride, Glycerol, Methocel, Propylene Glycol, Sodium Chloride

Questions or Comments?

Call 877-323-9184 toll-free M-F 9:00am to 5:00pm CT.

PATIENT COUNSELING INFORMATION

Venodol™
ROLL-ON

CONSUMER INFORMATION

FREQUENTLY ASKED QUESTIONS

What is Venodol?

Venodol is an anti-inflammatory, non-opioid, non-steroidal, non-addictive analgesic derived from cobra venom. Venodol does not contain other non-steroidal anti-inflammatory drugs (NSAIDs) such as aspirin, naproxen sodium or ibuprofen, and does not contain acetaminophen. Venodol is specifically intended for the relief of moderate to severe chronic pain.

What is HPUS?

HPUS is the acronym for the Homeopathic Pharmacopoeia of the United States. Per the HPUS, Venodol's active ingredient, cobra venom, is an analgesic.

Is Venodol addictive?

No. Venodol is not addictive as it is not an opiate-based medication.

Can I overdose from Venodol?

No. Venodol is non-toxic, so overdosing is not a possibility if used as directed.

Are there side effects with Venodol?

Few side effects have been reported but may include headache, localized itchiness or mild rash.

Can Venodol be used with other analgesic medications?

Yes. In clinical use, the active ingredient in Venodol showed no contraindications with any other analgesic products.

CLINICAL HISTORY OF COBRA VENOM

In the Homeopathic Pharmacopoeia of the United States (HPUS) the active ingredient in Venodol, cobra venom (Naja), is recognized in Clarke's Dictionary of Practical Mateira Medica principally as an analgesic.

The venom from a variety of common cobras in Asia (Naja naja or Naja tripudians) has been reported to be effective in standard animal models of pain and inflammation.

Numerous clinical studies with these venoms have reported relief of chronic pain in subjects with a spectrum of persistent conditions.

DIRECTIONS FOR USE

- Use 3 to 4 times per day. Allow at least two weeks for full effect
- Apply liberally on affected areas
- Rub thoroughly until fully absorbed
- Use as-needed when pain relief is achieved

ACTIVE INGREDIENT

Cobra Venom (Naja naja) 4x (0.1 mg/gm) HPUS

INACTIVE INGREDIENTS

Benzalkonium Chloride, Glycerol, Methocel, Propylene Glycol, Sodium Chloride

USES

Temporarily relieves persistent pain associated with inflammation and localized pain associated with strain.

WARNINGS

For External Use Only

- Do not use on broken skin.
- If symptoms persist or worsen, discontinue use and seek medical attention.
- Avoid contact with eyes. If product gets into eyes, flush with water and seek medical attention.
- If an allergic reaction occurs, discontinue use and seek medical attention.
- If rash, redness, irritation, or itching occurs, discontinue use.
- If pregnant or breastfeeding, ask a health professional before use.
- If swallowed, get medical help or contact a Poison Control Center right away.
- Keep out of reach of children.

STORAGE

Store at 50° to 80°F (10°C to 26°C). Use within 90 days of opening.

OTHER INFORMATION

- This product is NOT intended to treat disease.
- This product is not effective for relieving osteoarthritis pain.

WHAT IS CHRONIC PAIN?

Chronic pain is any pain lasting for more than 12 weeks. Chronic pain may result from an initial injury, but people can suffer from chronic pain without any past injuries, traumas or illness. Chronic pain can lead to other health problems, including loss of appetite, fatigue, sleep disturbance, and mood changes.

WHAT SHOULD I EXPECT WHEN TAKING VENODOL?

Venodol builds up in your system over time so it may take up to two weeks for your body to feel the full effect and, therefore, it is important that the product be used as directed to maximize the potential for achieving pain relief. Your response time to Venodol will vary depending on the severity and nature of your pain. Once pain relief is achieved, the application frequency can be adjusted to an as-needed basis. Venodol is not suitable for the relief of acute (sudden onset) pain.

QUESTIONS OR COMMENTS?

Call 877-323-9184 or visit www.venodol.com

Manufactured for Caretta Therapeutics, LLC, 11147 Aurora Avenue, Urbandale, IA 50322